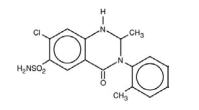 DRUG LABEL: Unknown
Manufacturer: Celltech Pharmaceuticals, Inc.
Category: prescription | Type: Human prescription drug label
Date: 20060112

Mykrox® Tablets
(metolazone tablets, USP)

DO NOT INTERCHANGE:

MYKROX TABLETS ARE A RAPIDLY AVAILABLE FORMULATION OF METOLAZONE FOR ORAL ADMINISTRATION. MYKROX TABLETS AND OTHER FORMULATIONS OF METOLAZONE THAT SHARE ITS MORE RAPID AND COMPLETE BIOAVAILABILITY ARE NOT THERAPEUTICALLY EQUIVALENT TO ZAROXOLYN® TABLETS AND OTHER FORMULATIONS OF METOLAZONE THAT SHARE ITS SLOW AND INCOMPLETE BIOAVAILABILITY. FORMULATIONS BIOEQUIVALENT TO MYKROX AND FORMULATIONS BIOEQUIVALENT TO ZAROXOLYN SHOULD NOT BE INTERCHANGED FOR ONE ANOTHER.

DESCRIPTION

MYKROX Tablets (metolazone tablets, USP) for oral administration contain ½ mg of metolazone, USP, a diuretic/saluretic/antihypertensive drug of the quinazoline class.

Metolazone has the molecular formula C16H16ClN3O3S, the chemical name 7-chloro-1, 2, 3, 4-tetrahydro-2-methyl-3-(2-methylphenyl)-4-oxo-6-quinazolinesulfonamide, and a molecular weight of 365.83. The structural formula is:

Metolazone is only sparingly soluble in water, but more soluble in plasma, blood, alkali, and organic solvents.

Inactive Ingredients: Dibasic calcium phosphate, magnesium stearate, microcrystalline cellulose, pregelatinized starch, sodium starch glycolate.

CLINICAL PHARMACOLOGY

MYKROX (metolazone) is a quinazoline diuretic, with properties generally similar to the thiazide diuretics. The actions of MYKROX result from interference with the renal tubular mechanism of electrolyte reabsorption. MYKROX acts primarily to inhibit sodium reabsorption at the cortical diluting site and to a lesser extent in the proximal convoluted tubule. Sodium and chloride ions are excreted in approximately equivalent amounts. The increased delivery of sodium to the distal tubular exchange site results in increased potassium excretion. MYKROX does not inhibit carbonic anhydrase. A proximal action of metolazone has been shown in humans by increased excretion of phosphate and magnesium ions and by a markedly increased fractional excretion of sodium in patients with severely compromised glomerular filtration. This action has been demonstrated in animals by micropuncture studies.

The antihypertensive mechanism of action of metolazone is not fully understood but is presumed to be related to its saluretic and diuretic properties.

In two double-blind, controlled clinical trials of MYKROX Tablets, the maximum effect on mean blood pressure was achieved within 2 weeks of treatment and showed some evidence of an increased response at 1 mg compared to ½ mg. There was no indication of an increased response with 2 mg.

After six weeks of treatment, the mean fall in serum potassium was 0.42 mEq/L at ½ mg, 0.66 mEq/L at 1 mg, and 0.7 mEq/L at 2 mg. Serum uric acid increased by 1.1 to 1.4 mg/dL at increasing doses. There were small falls in serum sodium and chloride and a 1.3-2.1 mg/dL increase in BUN at increasing doses.

The rate and extent of absorption of metolazone from MYKROX Tablets were equivalent to those from an oral solution of metolazone. Peak blood levels are obtained within 2 to 4 hours of oral administration with an elimination half-life of approximately 14 hours. MYKROX Tablets have been shown to produce blood levels that are dose proportional between ½ -2 mg. Steady state blood levels are usually reached in 4-5 days.

In contrast, other formulations of metolazone produce peak blood concentrations approximately 8 hours following oral administration; absorption continues for an additional 12 hours.

INDICATIONS AND USAGE

MYKROX Tablets are indicated for the treatment of hypertension, alone or in combination with other antihypertensive drugs of a different class.

MYKROX TABLETS HAVE NOT BEEN EVALUATED FOR THE TREATMENT OF CONGESTIVE HEART FAILURE OR FLUID RETENTION DUE TO RENAL OR HEPATIC DISEASE AND THE CORRECT DOSAGE FOR THESE CONDITIONS AND OTHER EDEMA STATES HAS NOT BEEN ESTABLISHED.

SINCE A SAFE AND EFFECTIVE DIURETIC DOSE HAS NOT BEEN ESTABLISHED, MYKROX TABLETS SHOULD NOT BE USED WHEN DIURESIS IS DESIRED.

Usage in Pregnancy

The routine use of diuretics in an otherwise healthy woman is inappropriate and exposes mother and fetus to unnecessary hazard. Diuretics do not prevent development of toxemia of pregnancy, and there is no evidence that they are useful in the treatment of developed toxemia (see PRECAUTIONS).

Edema during pregnancy may arise from pathologic causes or from the physiologic and mechanical consequences of pregnancy. MYKROX is not indicated for the treatment of edema in pregnancy. Dependent edema in pregnancy resulting from restriction of venous return by the expanded uterus is properly treated through elevation of the lower extremities and use of support hose; use of diuretics to lower intravascular volume in this case is illogical and unnecessary. There is hypervolemia during normal pregnancy which is harmful to neither the fetus nor the mother (in the absence of cardiovascular disease), but which is associated with edema, including generalized edema, in the majority of pregnant women. If this edema produces discomfort, increased recumbency will often provide relief. In rare instances, this edema may cause extreme discomfort which is not relieved by rest. In these cases, a short course of diuretics may be appropriate.

CONTRAINDICATIONS

Anuria, hepatic coma or precoma, known allergy or hypersensitivity to metolazone.

WARNINGS

Rapid Onset Hyponatremia and/or Hypokalemia

Rarely, the rapid onset of severe hyponatremia and/or hypokalemia has been reported following initial doses of thiazide and non-thiazide diuretics. When symptoms consistent with severe electrolyte imbalance appear rapidly, drug should be discontinued and supportive measures should be initiated immediately. Parenteral electrolytes may be required. Appropriateness of therapy with this class of drugs should be carefully reevaluated.

Hypokalemia

Hypokalemia may occur with consequent weakness, cramps, and cardiac dysrhythmias. Serum potassium should be determined at regular and appropriate intervals, and dose reduction, potassium supplementation or addition of a potassium-sparing diuretic instituted whenever indicated. Hypokalemia is a particular hazard in patients who are digitalized or who have or have had a ventricular arrhythmia; dangerous or fatal arrhythmias may be precipitated. Hypokalemia is dose related.

In controlled clinical trials, 1.5% of patients taking ½ mg and 3.1% of patients taking 1 mg of MYKROX daily developed clinical hypokalemia (defined as hypokalemia accompanied by signs or symptoms); 21% of the patients taking ½ mg and 30% of the patients taking 1 mg of MYKROX daily developed hypokalemia (defined as a serum potassium concentration below 3.5 mEq/L); in another controlled clinical trial in which the patients started therapy with a serum potassium level greater than 4.0 mEq/L, 8% of patients taking ½ mg of MYKROX daily developed hypokalemia (defined as a serum potassium concentration below 3.5 mEq/L).

Concomitant Therapy

Lithium

In general, diuretics should not be given concomitantly with lithium because they reduce its renal clearance and add a high risk of lithium toxicity. Read prescribing information for lithium preparations before use of such concomitant therapy.

Furosemide

Unusually large or prolonged losses of fluids and electrolytes may result when metolazone is administered concomitantly to patients receiving furosemide (see PRECAUTIONS, Drug Interactions).

Other Antihypertensive Drugs

When MYKROX Tablets are used with other antihypertensive drugs, particular care must be taken to avoid excessive reduction of blood pressure, especially during initial therapy.

Cross-Allergy

Cross-allergy may occur when MYKROX Tablets are given to patients known to be allergic to sulfonamide-derived drugs, thiazides, or quinethazone.

Sensitivity Reactions

Sensitivity reactions (e.g., angioedema, bronchospasm) may occur with or without a history of allergy or bronchial asthma and may occur with the first dose of MYKROX.

PRECAUTIONS

DO NOT INTERCHANGE

MYKROX TABLETS ARE A RAPIDLY AVAILABLE FORMULATION OF METOLAZONE FOR ORAL ADMINISTRATION. MYKROX TABLETS AND OTHER FORMULATIONS OF METOLAZONE THAT SHARE ITS MORE RAPID AND COMPLETE BIOAVAILABILITY ARE NOT THERAPEUTICALLY EQUIVALENT TO ZAROXOLYN TABLETS AND OTHER FORMULATIONS OF METOLAZONE THAT SHARE ITS SLOW AND INCOMPLETE BIOAVAILABILITY. FORMULATIONS BIOEQUIVALENT TO MYKROX AND FORMULATIONS BIOEQUIVALENT TO ZAROXOLYN SHOULD NOT BE INTERCHANGED FOR ONE ANOTHER.

General

Fluid and Electrolytes

All patients receiving therapy with MYKROX Tablets should have serum electrolyte measurements done at appropriate intervals and be observed for clinical signs of fluid and/or electrolyte imbalance: namely, hyponatremia, hypochloremic alkalosis, and hypokalemia. In patients with severe edema accompanying cardiac failure or renal disease, a low-salt syndrome may be produced, especially with hot weather and a low-salt diet. Serum and urine electrolyte determinations are particularly important when the patient has protracted vomiting, severe diarrhea, or is receiving parenteral fluids. Warning signs of imbalance are: dryness of mouth, thirst, weakness, lethargy, drowsiness, restlessness, muscle pains or cramps, muscle fatigue, hypotension, oliguria, tachycardia, and gastrointestinal disturbances such as nausea and vomiting. Hyponatremia may occur at any time during long term therapy and, on rare occasions, may be life threatening.

The risk of hypokalemia is increased when larger doses are used, when diuresis is rapid, when severe liver disease is present, when corticosteroids are given concomitantly, when oral intake is inadequate or when excess potassium is being lost extrarenally, such as with vomiting or diarrhea.

Thiazide-like diuretics have been shown to increase the urinary excretion of magnesium; this may result in hypomagnesemia.

Glucose Tolerance

Metolazone may raise blood glucose concentrations possibly causing hyperglycemia and glycosuria in patients with diabetes or latent diabetes.

Hyperuricemia

MYKROX regularly causes an increase in serum uric acid and can occasionally precipitate gouty attacks even in patients without a prior history of them.

Azotemia

Azotemia, presumably prerenal azotemia, may be precipitated during the administration of MYKROX Tablets. If azotemia and oliguria worsen during treatment of patients with severe renal disease, MYKROX Tablets should be discontinued.

Renal Impairment

Use caution when administering MYKROX Tablets to patients with severely impaired renal function. As most of the drug is excreted by the renal route, accumulation may occur.

Orthostatic Hypotension

Orthostatic hypotension may occur; this may be potentiated by alcohol, barbiturates, narcotics, or concurrent therapy with other antihypertensive drugs. In controlled clinical trials, 1.4% of patients treated with MYKROX Tablets (½ mg) had orthostatic hypotension; this effect was not reported in the placebo group.

Hypercalcemia

Hypercalcemia may infrequently occur with metolazone, especially in patients taking high doses of vitamin D or with high bone turnover states, and may signify hidden hyperparathyroidism. Metolazone should be discontinued before tests for parathyroid function are performed.

Systemic Lupus Erythematosus

Thiazide diuretics have exacerbated or activated systemic lupus erythematosus and this possibility should be considered with MYKROX Tablets.

Information for Patients

Patients should be informed of possible adverse effects, advised to take the medication as directed, and promptly report any possible adverse reactions to the treating physician.

Drug Interactions

Diuretics

Furosemide and probably other loop diuretics given concomitantly with metolazone can cause unusually large or prolonged losses of fluid and electrolytes (see WARNINGS).

Other Antihypertensives

When MYKROX Tablets are used with other antihypertensive drugs, care must be taken, especially during initial therapy. Dosage adjustments of other antihypertensives may be necessary.

Alcohol, Barbiturates, and Narcotics

The hypotensive effects of these drugs may be potentiated by the volume contraction that may be associated with metolazone therapy.

Digitalis Glycosides

Diuretic-induced hypokalemia can increase the sensitivity of the myocardium to digitalis. Serious arrhythmias can result.

Corticosteroids or ACTH

May increase the risk of hypokalemia and increase salt and water retention.

Lithium

Serum lithium levels may increase (see WARNINGS).

Curariform Drugs

Diuretic-induced hypokalemia may enhance neuromuscular blocking effects of curariform drugs (such as tubocurarine) – the most serious effect would be respiratory depression which could proceed to apnea. Accordingly, it may be advisable to discontinue MYKROX® Tablets (metolazone tablets, USP) three days before elective surgery.

Salicylates and Other Non-Steroidal Anti-Inflammatory Drugs

May decrease the antihypertensive effects of MYKROX Tablets.

Sympathomimetics

Metolazone may decrease arterial responsiveness to norepinephrine, but this diminution is not sufficient to preclude effectiveness of the pressor agent for therapeutic use.

Insulin and Oral Antidiabetic Agents

See Glucose Tolerance under PRECAUTIONS, General.

Methenamine

Efficacy may be decreased due to urinary alkalizing effect of metolazone.

Anticoagulants

Metolazone, as well as other thiazide-like diuretics, may affect the hypoprothrombinemic response to anticoagulants; dosage adjustments may be necessary.

Drug/Laboratory Test Interactions

None reported.

Carcinogenesis, Mutagenesis, Impairment of Fertility

Mice and rats administered metolazone 5 days/week for up to 18 and 24 months, respectively, at daily doses of 2, 10, and 50 mg/kg, exhibited no evidence of a tumorigenic effect of the drug. The small number of animals examined histologically and poor survival in the mice limit the conclusions that can be reached from these studies.

Metolazone was not mutagenic in vitro in the Ames Test using Salmonella typhimurium strains TA-97, TA-98, TA-100, TA-102, and TA-1535.

Reproductive performance has been evaluated in mice and rats. There is no evidence that metolazone possesses the potential for altering reproductive capacity in mice. In a rat study, in which males were treated orally with metolazone at doses of 2, 10, and 50 mg/kg for 127 days prior to mating with untreated females, an increased number of resorption sites was observed in dams mated with males from the 50 mg/kg group. In addition, the birth weight of offspring was decreased and the pregnancy rate was reduced in dams mated with males from the 10 and 50 mg/kg groups.

Pregnancy

Teratogenic Effects

Pregnancy Category B

Reproduction studies performed in mice, rabbits, and rats treated during the appropriate period of gestation at doses up to 50 mg/kg/day have revealed no evidence of harm to the fetus due to metolazone. There are, however, no adequate and well-controlled studies in pregnant women. Because animal reproduction studies are not always predictive of human response, MYKROX Tablets should be used during pregnancy only if clearly needed. Metolazone crosses the placental barrier and appears in cord blood.

Non-Teratogenic Effects

The use of MYKROX Tablets in pregnant women requires that the anticipated benefit be weighed against possible hazards to the fetus. These hazards include fetal or neonatal jaundice, thrombocytopenia, and possibly other adverse reactions which have occurred in the adult. It is not known what effect the use of the drug during pregnancy has on the later growth, development, and functional maturation of the child. No such effects have been reported with metolazone.

Labor and Delivery

Based on clinical studies in which women received metolazone in late pregnancy until the time of delivery, there is no evidence that the drug has any adverse effects on the normal course of labor or delivery.

Nursing Mothers

Metolazone appears in breast milk. Because of the potential for serious adverse reactions in nursing infants from metolazone, a decision should be made whether to discontinue nursing or to discontinue the drug, taking into account the importance of the drug to the mother.

Pediatric Use

Safety and effectiveness of MYKROX Tablets in pediatric patients have not been established, and such use is not recommended.

Geriatric Use

Clinical studies of MYKROX did not include sufficient numbers of subjects aged 65 and over to determine whether they respond differently from younger subjects. Other reported clinical experience has not identified differences in responses between the elderly and younger patients. In general, dose selection for an elderly patient should be cautious, usually starting at the low end of the dosing range, reflecting the greater frequency of decreased hepatic, renal, or cardiac function, and of concomitant disease or other drug therapy.

This drug is known to be substantially excreted by the kidney, and the risk of toxic reactions to this drug may be greater in patients with impaired renal function. Because elderly patients are more likely to have decreased renal function, care should be taken in dose selection, and it may be useful to monitor renal function.

ADVERSE REACTIONS

Adverse experience information is available from more than 14 years of accumulated marketing experience with other formulations of metolazone for which reliable quantitative information is lacking and from controlled clinical trials with MYKROX from which incidences can be calculated.

In controlled clinical trials with MYKROX, adverse experiences resulted in discontinuation of therapy in 6.7-6.8% of patients given ½ to 1 mg of MYKROX.

Adverse experiences occurring in controlled clinical trials with MYKROX with an incidence of >2%, whether or not considered drug-related, are summarized in the following table.

Incidence of Adverse Experiences Volunteered or Elicited (by Patient in Percent)*
 | MYKROX n = 226†
Dizziness (lightheadedness) | 10.2
Headaches | 9.3
Muscle Cramps | 5.8
Fatigue (malaise, lethargy, lassitude) | 4.4
Joint Pain, swelling | 3.1
Chest Pain (precordial discomfort) | 2.7
* Percent of patients reporting an adverse experience one or more times.
† All doses combined (½, 1, and 2 mg).

Some of the adverse effects reported in association with MYKROX also occur frequently in untreated hypertensive patients, such as headache and dizziness, which occurred in 14.8 and 7.4% of patients in a smaller parallel placebo group.

The following adverse effects were reported in less than 2% of the MYKROX treated patients.

Cardiovascular

Cold extremities, edema, orthostatic hypotension, palpitations.

Central and Peripheral Nervous System

Anxiety, depression, dry mouth, impotence, nervousness, neuropathy, weakness, “weird” feeling.

Dermatological

Pruritus, rash, skin dryness.

Eyes, Ears, Nose, Throat

Cough, epistaxis, eye itching, sinus congestion, sore throat, tinnitus.

Gastrointestinal

Abdominal discomfort (pain, bloating), bitter taste, constipation, diarrhea, nausea, vomiting.

Genitourinary

Nocturia.

Musculoskeletal

Back pain.

Other Adverse Experiences

Adverse experiences reported with other marketed metolazone formulations and most thiazide diuretics, for which quantitative data are not available, are listed in decreasing order of severity within body systems. Several are single or rare occurrences.

Cardiovascular

excessive volume depletion, hemoconcentration, venous thrombosis.

Central and Peripheral Nervous System

syncope, paresthesias, drowsiness, restlessness (sometimes resulting in insomnia).

Dermatologic/Hypersensitivity

toxic epidermal necrolysis (TEN), Stevens-Johnson Syndrome, necrotizing angiitis (cutaneous vasculitis), skin necrosis, purpura, petechiae, dermatitis, photosensitivity, urticaria, pruritus, skin rashes.

Gastrointestinal

hepatitis, intrahepatic cholestatic jaundice, pancreatitis, anorexia, nausea, diarrhea, abdominal pain.

Hematologic

aplastic (hypoplastic) anemia, agranulocytosis, leukopenia, thrombocytopenia.

Metabolic

hypokalemia (see WARNINGS, Hypokalemia), hyponatremia, hyperuricemia, hypochloremia, hypochloremic alkalosis, hyperglycemia, glycosuria, increase in serum urea nitrogen (BUN) or creatinine, hypophosphatemia, hypomagnesemia, hypercalcemia.

Musculoskeletal

acute gouty attacks.

Other

transient blurred vision, chills.

In addition, rare adverse experiences reported in association with similar antihypertensive-diuretics but not reported to date for metolazone include: sialadenitis, xanthopsia, respiratory distress (including pneumonitis), and anaphylactic reactions. These experiences could occur with clinical use of metolazone.

OVERDOSAGE

Intentional overdosage has been reported rarely with metolazone and similar diuretic drugs.

Signs and Symptoms

Orthostatic hypotension, dizziness, drowsiness, syncope, electrolyte abnormalities, hemoconcentration and hemodynamic changes due to plasma volume depletion may occur. In some instances depressed respiration may be observed. At high doses, lethargy of varying degree may progress to coma within a few hours. The mechanism of CNS depression with thiazide overdosage is unknown. Also, GI irritation and hypermotility may occur. Temporary elevation of BUN has been reported, especially in patients with impairment of renal function. Serum electrolyte changes and cardiovascular and renal function should be closely monitored.

Treatment

There is no specific antidote available but immediate evacuation of stomach contents is advised. Dialysis is not likely to be effective. Care should be taken when evacuating the gastric contents to prevent aspiration, especially in the stuporous or comatose patient. Supportive measures should be initiated as required to maintain hydration, electrolyte balance, respiration, and cardiovascular and renal function.

DOSAGE AND ADMINISTRATION

Therapy should be individualized according to patient response.

For initial treatment of mild to moderate hypertension, the recommended dose is one MYKROX Tablet (½ mg) once daily, usually in the morning. If patients are inadequately controlled with one ½ mg tablet, the dose can be increased to two MYKROX Tablets (1 mg) once a day. An increase in hypokalemia may occur. Doses larger than 1 mg do not give increased effectiveness.

The same dose titration is necessary if MYKROX Tablets are to be substituted for other dosage forms of metolazone in the treatment of hypertension.

If blood pressure is not adequately controlled with two MYKROX Tablets alone, the dose should not be increased; rather, another antihypertensive agent with a different mechanism of action should be added to therapy with MYKROX Tablets.

HOW SUPPLIED

MYKROX Tablets (metolazone tablets, USP), ½ mg are white, flat-faced, round tablets, debossed “MYKROX” on one side, and “½” on reverse side.

NDC 53014-847-71 Bottle of 100’s

Store at 25°C (77°F); excursions permitted to 15°-30°C (59°-86°F) [See USP Controlled Room Temperature]. Protect from light. Keep out of the reach of children.

Celltech Pharmaceuticals, Inc.
Rochester, NY 14623 USA

® Celltech Manufacturing, Inc.
© 2003, Celltech Pharmaceuticals, Inc.
All rights reserved.

Rev. 2/03
R528B